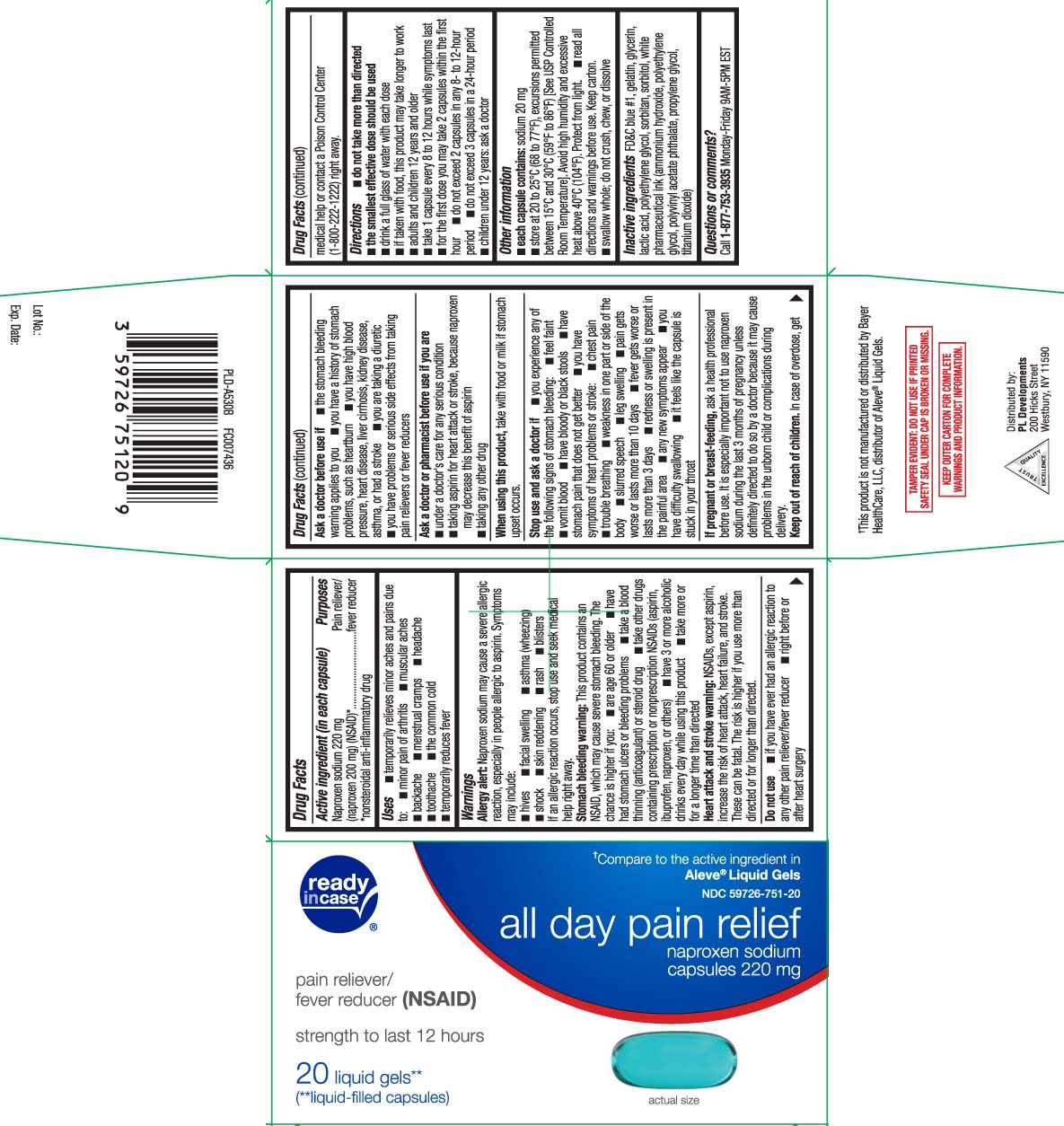 DRUG LABEL: Naproxen Sodium
NDC: 59726-751 | Form: CAPSULE
Manufacturer: P & L Development, LLC
Category: otc | Type: HUMAN OTC DRUG LABEL
Date: 20251117

ACTIVE INGREDIENTS: NAPROXEN SODIUM 220 mg/1 1
INACTIVE INGREDIENTS: FD&C BLUE NO. 1; GELATIN; GLYCERIN; LACTIC ACID; POLYETHYLENE GLYCOL, UNSPECIFIED; SORBITAN; SORBITOL

Drug Facts

Active ingredient (in each capsule)

Naproxen sodium 220 mg

(naproxen 200 mg) (NSAID)*

*nonsteroidal anti-inflammatory drug

Purposes

Pain reliever/fever reducer

Uses

- temporarily relieves minor aches and pains due to:
  - headache
  - muscular aches
  - minor pain of arthritis
  - toothache
  - backache
  - the common cold
  - menstrual cramps
- temporarily reduces fever

Warnings

Allergy alert: Naproxen sodium may cause a severe allergic reaction, especially in people allergic to aspirin. Symptoms may include:

- hives
- facial swelling
- asthma (wheezing)
- shock
- skin reddening
- rash
- blisters

If an allergic reaction occurs, stop use and seek medical help right away.

Stomach bleeding warning: This product contains an NSAID, which may cause severe stomach bleeding. The chance is higher if you:

- are age 60 or older
- have had stomach ulcers or bleeding problems
- take a blood thinning (anticoagulant) or steroid drug
- have 3 or more alcoholic drinks every day while using this product
- take other drugs containing prescription or nonprescription NSAIDs (aspirin, ibuprofen, naproxen, or others)
- take more or for a longer time than directed

Heart attack and stroke warning: NSAIDs, except aspirin, increase the risk of heart attack, heart failure, and stroke. These can be fatal. The risk is higher if you use more than directed or for longer than directed

Do not use

- if you have ever had an allergic reaction to any other pain reliever/fever reducer
- right before or after heart surgery

Ask a doctor before use if

- the stomach bleeding warning applies to you
- you have a history of stomach problems, such as heartburn
- you have high blood pressure, heart disease, liver cirrhosis, kidney disease, asthma, or had a stroke
- you have problems or serious side effects from taking pain relievers or fever reducers
- you are taking a diuretic

Ask a doctor or pharmacist before use if you are

- under a doctor’s care for any serious condition
- taking aspirin for heart attack or stroke, because naproxen may decrease this benefit of aspirin
- taking any other drug

When using this product

take with food or milk if stomach upset occurs

Stop use and ask a doctor if

- you experience any of the following signs of stomach bleeding:
  - feel faint
  - have bloody or black stools
  - vomit blood
  - have stomach pain that does not get better
- you have symptoms of heart problem or stroke:
  - chest pain
  - slurred speech
  - leg swelling
  - trouble breathing
  - weakness in one part or side of the body
- pain gets worse or lasts more than 10 days
- fever gets worse or lasts more than 3 days
- redness or swelling is present in the painful area
- any new symptoms appear
- you have difficulty swallowing
- it feels like the pill is stuck in your throat

If pregnant or breast-feeding,

ask a health professional before use. It is especially important not to use naproxen sodium during the last 3 months of pregnancy unless definitely directed to do so by a doctor because it may cause problems in the unborn child or complications during delivery.

Keep out of reach of children.

In case of overdose, get medical help or contact a Poison Control Center (1-800-222-1222) right away.

Directions

- do not take more than directed
- the smallest effective dose should be used
- drink a full glass of water with each dose
- if taken with food, this product may taken longer to work
- adults and children 12 years and older:
  - take 1 capsule every 8 to 12 hours while symptoms last
  - for the first dose you may take 2 tablets within the first hour
  - do not exceed 2 tablets in any 8- to 12-hour period
  - do not exceed 3 tablets in a 24-hour period
- children under 12 years: ask a doctor

Other information

- each tablet contains: sodium 20 mg
- store at 20º to 25°C (68º to 77°F), excursions permitted between 15ºC and 30ºC (59ºF to 86ºF) [See USP Controlled Room Temperature]. Avoid high humidity and excessive heat above 40°C (104°F). Protect from light.
- read all direction and warnings before use. Keep carton.
- swallow whole: do not crush, chew or dissolve

Inactive ingredients

FD&C blue #1, gelatin, glycerin, lactic acid, polyethylene glycol, sorbitan, sorbitol, white pharmaceutical ink

Questions or comments?

Call 1-877-753-3935 Monday-Friday 9AM-5PM EST

Principal Display Panel

†Compare to the active ingredient in Aleve® Liquid Gels

all day pain relief

Naproxen Sodium

capsules 220 mg

pain reliever / fever reducer (NSAID)

strength to last 12 hours

liquid gels**

(**liquid-filled capsules)

††This product is not manufactured or distributed by Bayer Healthcare, LLC, distributor of Aleve® Liquid Gels.

TAMPER EVIDENT: DO NOT USE IF PRINTED SAFETY SEAL UNDER CAP IS BROKEN OR MISSING

KEEP OUTER CARTON FOR COMPLETE WARNINGS AND PRODUCT INFORMATION

Distributed by:

PL Developments

200 Hicks Street

Westbury, NY 11590

Package Label

READYinCASE All Day Pain Relief Capsules